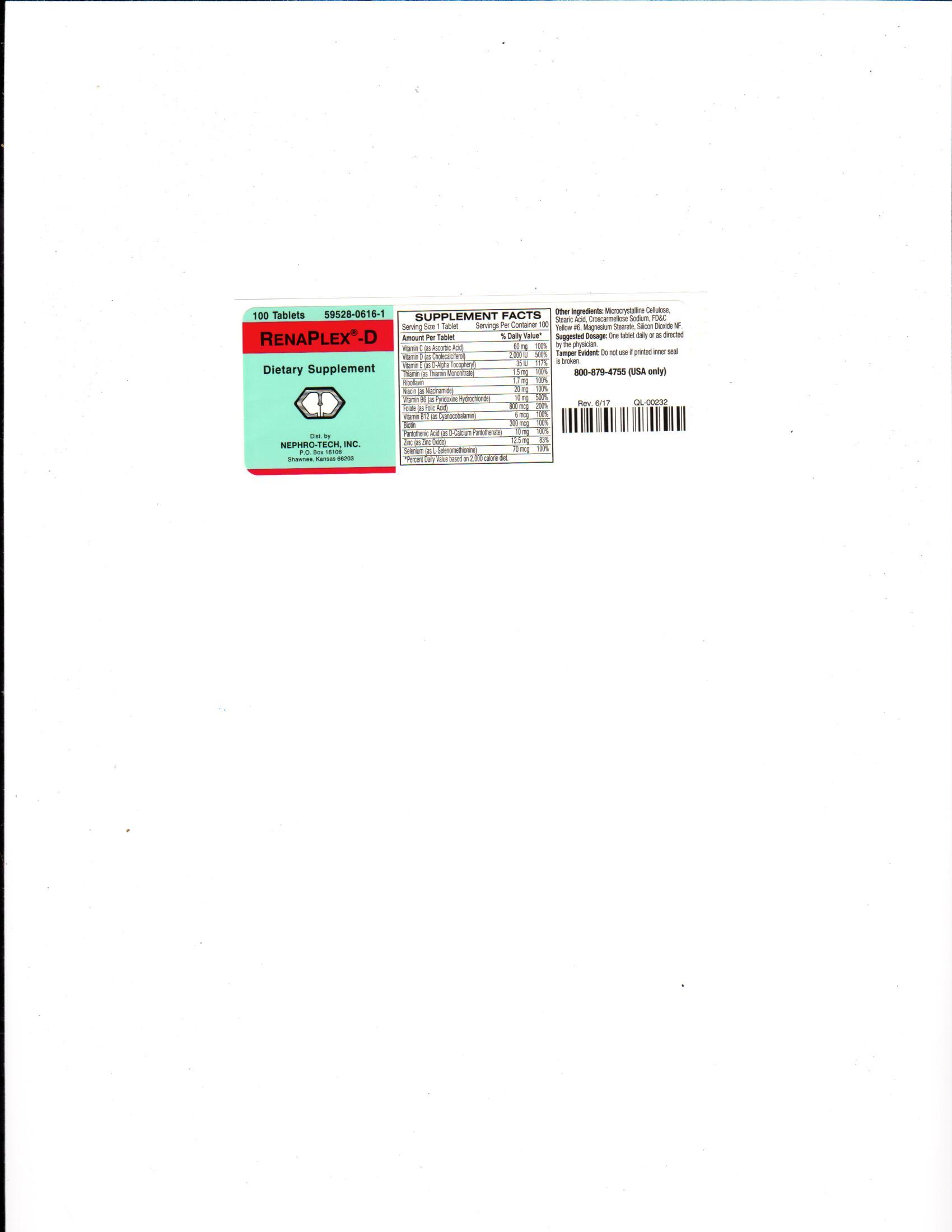 DRUG LABEL: RenaPlex-D
NDC: 59528-0616 | Form: TABLET, COATED
Manufacturer: Nephro-Tech, Inc.
Category: other | Type: Dietary Supplement
Date: 20210715

ACTIVE INGREDIENTS: ASCORBIC ACID 60 mg/1 1; CHOLECALCIFEROL 2000 [iU]/1 1; TOCOPHEROL 35 [iU]/1 1; THIAMINE 1500 ug/1 1; RIBOFLAVIN 1700 ug/1 1; NIACINAMIDE 20 mg/1 1; PYRIDOXINE HYDROCHLORIDE 10 mg/1 1; FOLIC ACID 800 ug/1 1; CYANOCOBALAMIN 6 ug/1 1; BIOTIN 300 ug/1 1; PANTOTHENIC ACID 10 mg/1 1; ZINC OXIDE 12.5 mg/1 1; SELENOMETHIONINE 70 ug/1 1

RenaPlex-D (ascorbic acid, cholecalciferol, d-alpha tocopheryl, thiamin mononitrate, riboflavin, niacamide, pyridoxine hydrochloride, folic acid, cyanocobalamin, biotin, pantothenic acid, zinc and selenium)

Suggested Dosage

One tablet daily or as directed by the physician.

Package Label/Principal Display Panel

9528-0616-1

RenaPlex-D

Dietary Supplement

100 Tablets

Dietary Supplement

Minerals and vitamins